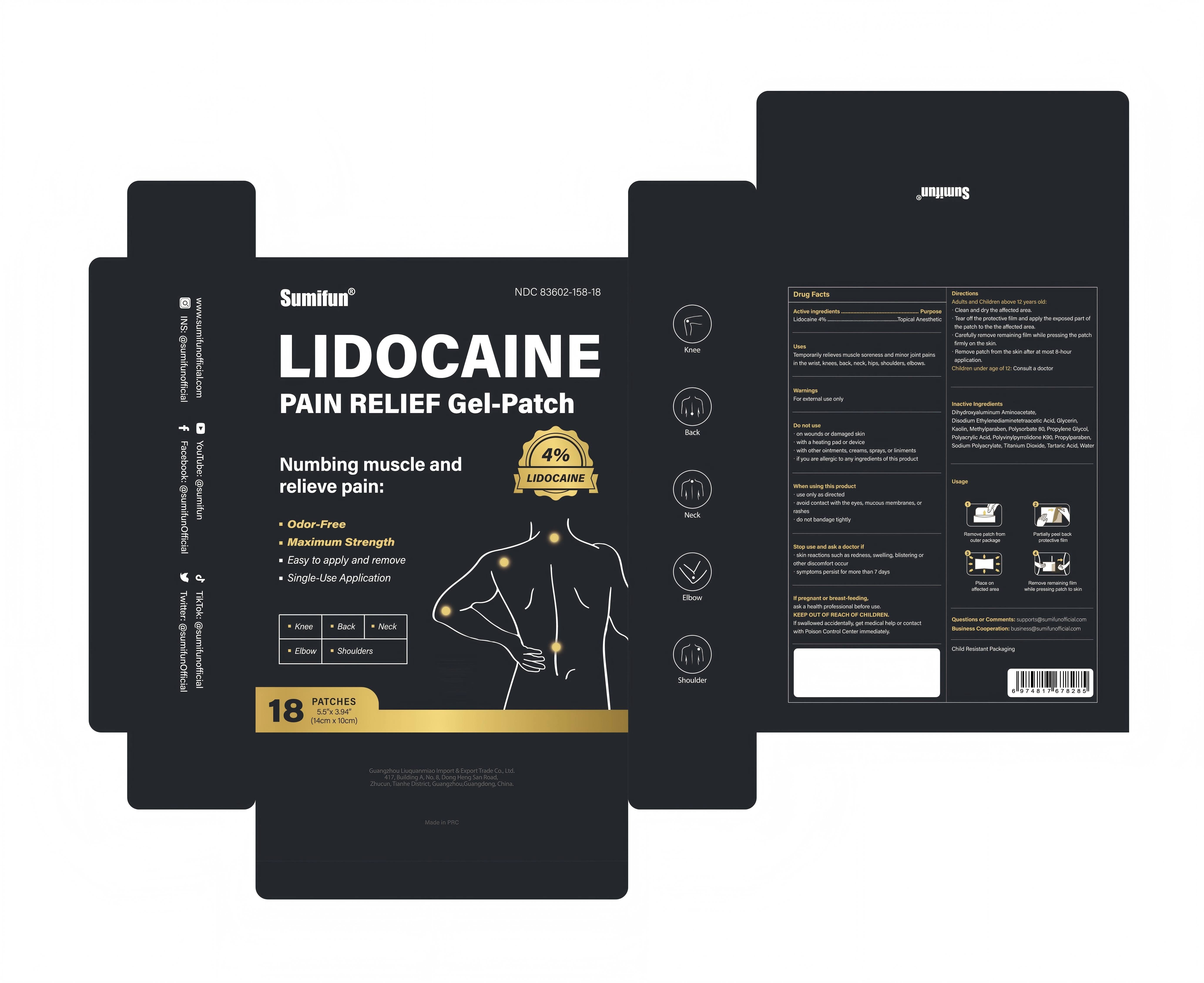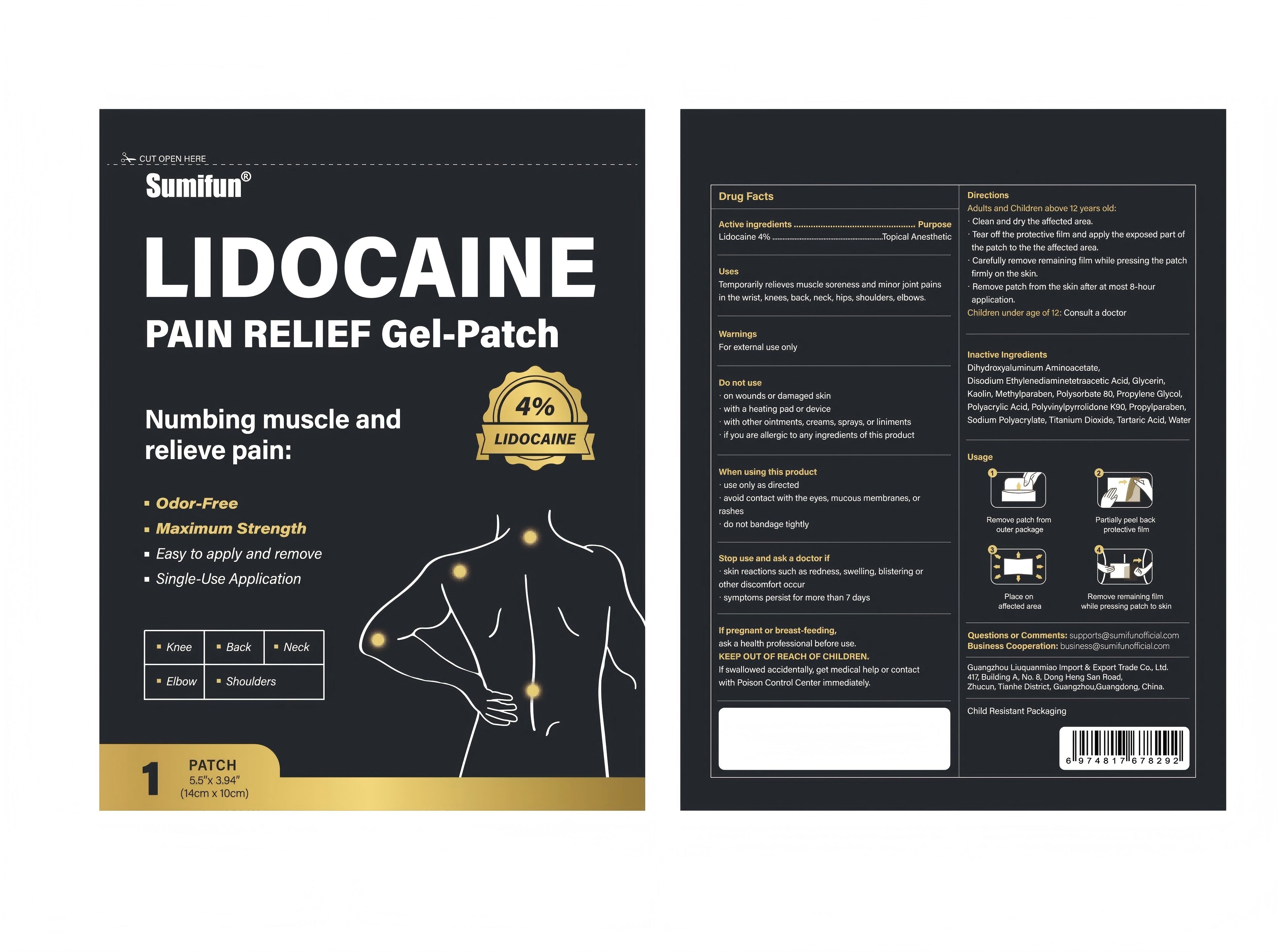 DRUG LABEL: LIDOCAINE PAIN RELIEF Gel-Patch
NDC: 83602-158 | Form: PATCH
Manufacturer: Guangzhou Liuquanmiao Import & Export Trade Co., Ltd.
Category: otc | Type: HUMAN OTC DRUG LABEL
Date: 20250729

ACTIVE INGREDIENTS: LIDOCAINE 0.04 g/1 g
INACTIVE INGREDIENTS: EDETATE DISODIUM; KAOLIN; TARTARIC ACID; WATER; PROPYLENE GLYCOL; POLYACRYLIC ACID (250000 MW); SODIUM POLYACRYLATE (2500000 MW); TITANIUM DIOXIDE; POLYSORBATE 80; GLYCERIN; POVIDONE K90; METHYLPARABEN; PROPYLPARABEN; DIHYDROXYALUMINUM AMINOACETATE ANHYDROUS

Liuquanmiao, LIDOCAINE PAIN RELIEF Gel-Patch, Lidocaine 4%, 18 Patches

Active ingredients

Lidocaine 4% ...... Purpose: Topical Analgesic

Purpose

Topical Anesthetic

Uses

Temporarily relieves muscle soreness and minor joint pains in the wrist, knees, back, neck, hips, shoulders, elbows.

Warnings

For external use only

Do not use

- on wounds or damaged skin
- with a heating pad or device
- with other ointments, creams, sprays, or liniments
- if you are allergic to any ingredients of this product

When using this product

- use only as directed
- avoid contact with the eyes, mucous membranes, or rashes
- do not bandage tightly

Stop use ... if

- skin reactions such as redness, swelling, blistering or other discomfort occur
- symptoms persist for more than 7 days

... ask a doctor if

- skin reactions such as redness, swelling, blistering or other discomfort occur
- symptoms persist for more than 7 days

If pregnant or breast-feeding

ask a health professional before use.

KEEP OUT OF REACH OF CHILDREN

If swallowed accidentally, get medical help or contact with Poison Control Center immediately.

Directions

Adults and Children above 12 years old:

- Clean and dry the affected area.
- Tear off the proctive film and apply the exposed part of the patch to the affected area.
- Carefully remove remaining film while pressing the patch firmly on the skin.
- Remove patch from the skin after at most 8-hour application.

Children under age of 12: Consult a doctor

Inactive Ingredients

Dihydroxyaluminum Aminoacetate, Disodium Ethylenediaminetetraacetic Acid, Glycerin, Kaolin, Methylparaben, Polysorbate 80, Propylene Glycol, Polyacrylic Acid, Polyvinylpyrrolidone K90, Propylparaben, Sodium Polyacrylate, Tartaric Acid, Titanium Dioxide, Water

Questions or Comments

supports@sumifunofficial.com

83602-158-18

PACKAGE LABEL.PRINCIPAL DISPLAY PANEL